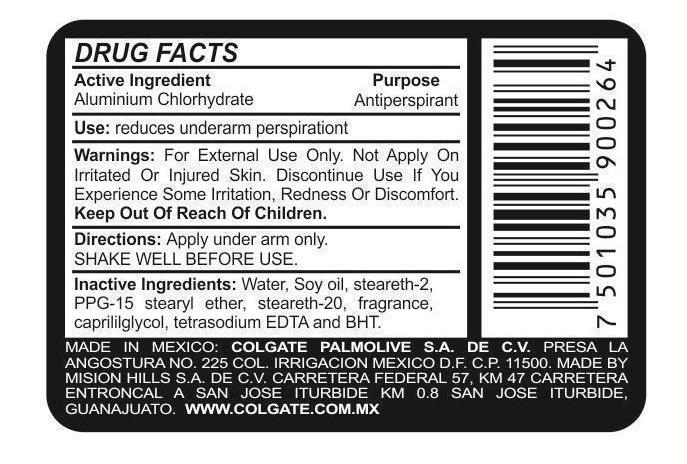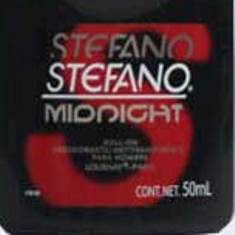 DRUG LABEL: Stefano Midnight
NDC: 69772-030 | Form: LIQUID
Manufacturer: Teresa Cecena DBA Genesis
Category: otc | Type: HUMAN OTC DRUG LABEL
Date: 20150602

ACTIVE INGREDIENTS: ALUMINUM CHLOROHYDRATE 50 g/100 mL
INACTIVE INGREDIENTS: STEARETH-20; CAPRYLYL GLYCOL; EDETATE SODIUM; BUTYLATED HYDROXYTOLUENE; STEARETH-2; PPG-15 STEARYL ETHER; WATER

ACTIVE INGREDIENT

Aluminum Chlorohydrate

Purpose:

Antiperspirant

Keep Out of reach of children

Use:

REDUCES UNDERARM PERSPERATION

WARNINGS

FOR EXTERNAL USE ONLY

WARNINGS AND PRECAUTIONS

DO NOT APPLY ON IRRITATED OR IN JURED SKIN

DISCONTINUE USE IF YOU EXPERIENCE SOME IRRITATION, REDNESS OR DISCOMFORT.

INDICATIONS AND USAGE

APPLY UNDER ARM ONLY

SHAKE WELL BEFORE USE

INACTIVE INGREDIENT

WATER, SOY OIL, STEARTH-2, PPG-15 STEARYL ETHER, STEARETH-20,FRAGANCE,CAPRYLYLGLYCOL,TETRASOSIUM EDTA, AND BHT